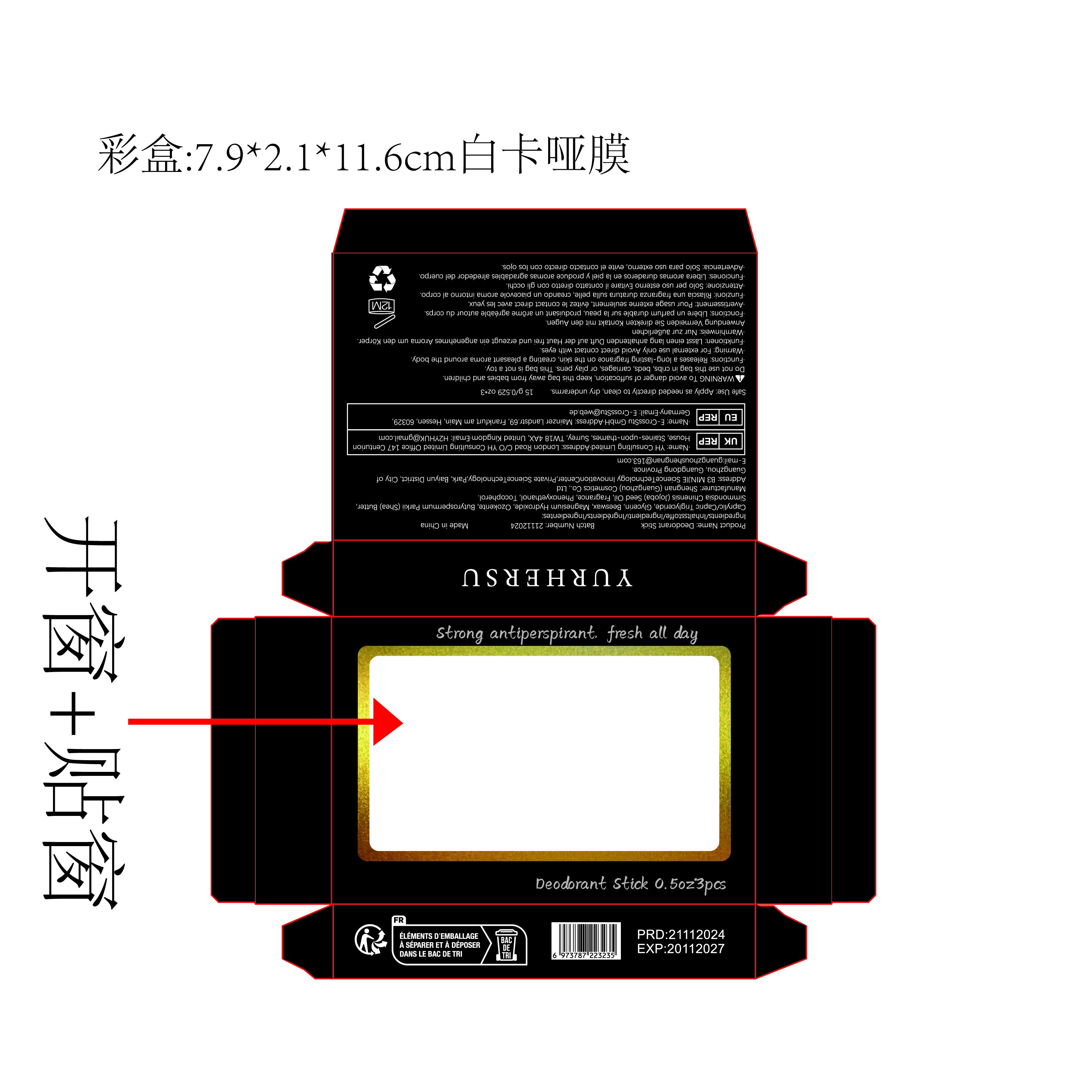 DRUG LABEL: DeodorantStick
NDC: 84019-013 | Form: CREAM
Manufacturer: Shengnan (Guangzhou) Cosmetics Co., LTD
Category: otc | Type: HUMAN OTC DRUG LABEL
Date: 20241204

ACTIVE INGREDIENTS: BUTYROSPERMUM PARKII (SHEA) BUTTER 100 mg/1 g
INACTIVE INGREDIENTS: BEESWAX; PHENOXYETHANOL; TOCOPHEROL; CAPRYLIC/CAPRIC TRIGLYCERIDE; SIMMONDSIA CHINENSIS (JOJOBA) SEED OIL; MAGNESIUM HYDROXIDE; GLYCERIN

WARNINGS

avoid danger of suffocation, keep this bag away from babies and children.

PURPOSE

Deodorant

Stop use and ask doctor if rash occurs.

ACTIVE INGREDIENT

BUTYROSPERMUM PARKII (SHEA) BUTTER

WHEN USING

Do not apply to wounds or damaged skin.

INACTIVE INGREDIENT

Caprylic/Capric Triglyceride
Glycerin
Beeswax
Ozokerite
Simmondsia Chinensis (Jojoba) Seed Oil
Fragrance
Phenoxyethanol
Tocopherol

DOSAGE AND ADMINISTRATION

Apply 1-2 times a day

INDICATIONS AND USAGE

Releases a long-lasting fragrance on the skin.
creating a pleasant aroma around the body